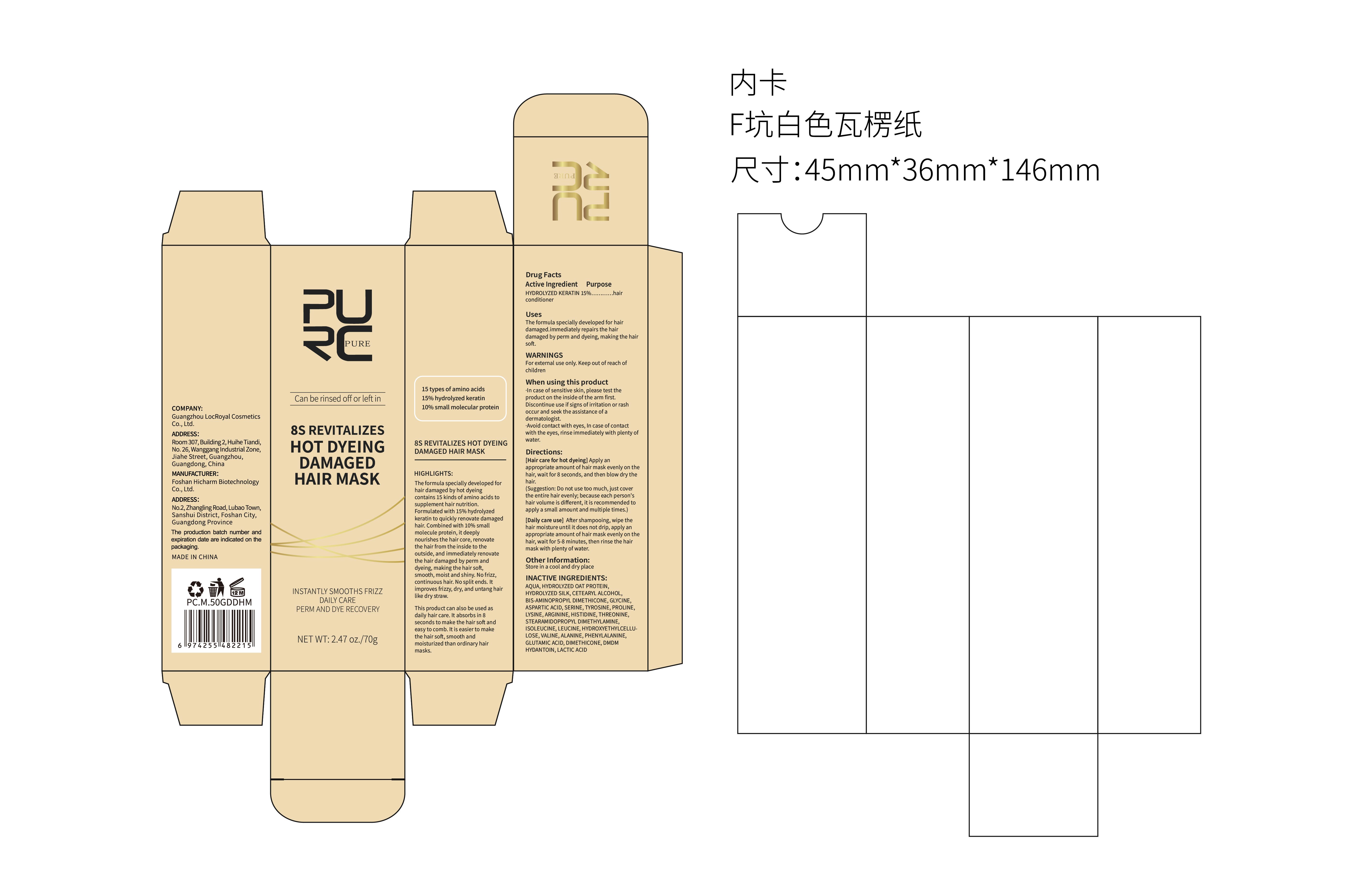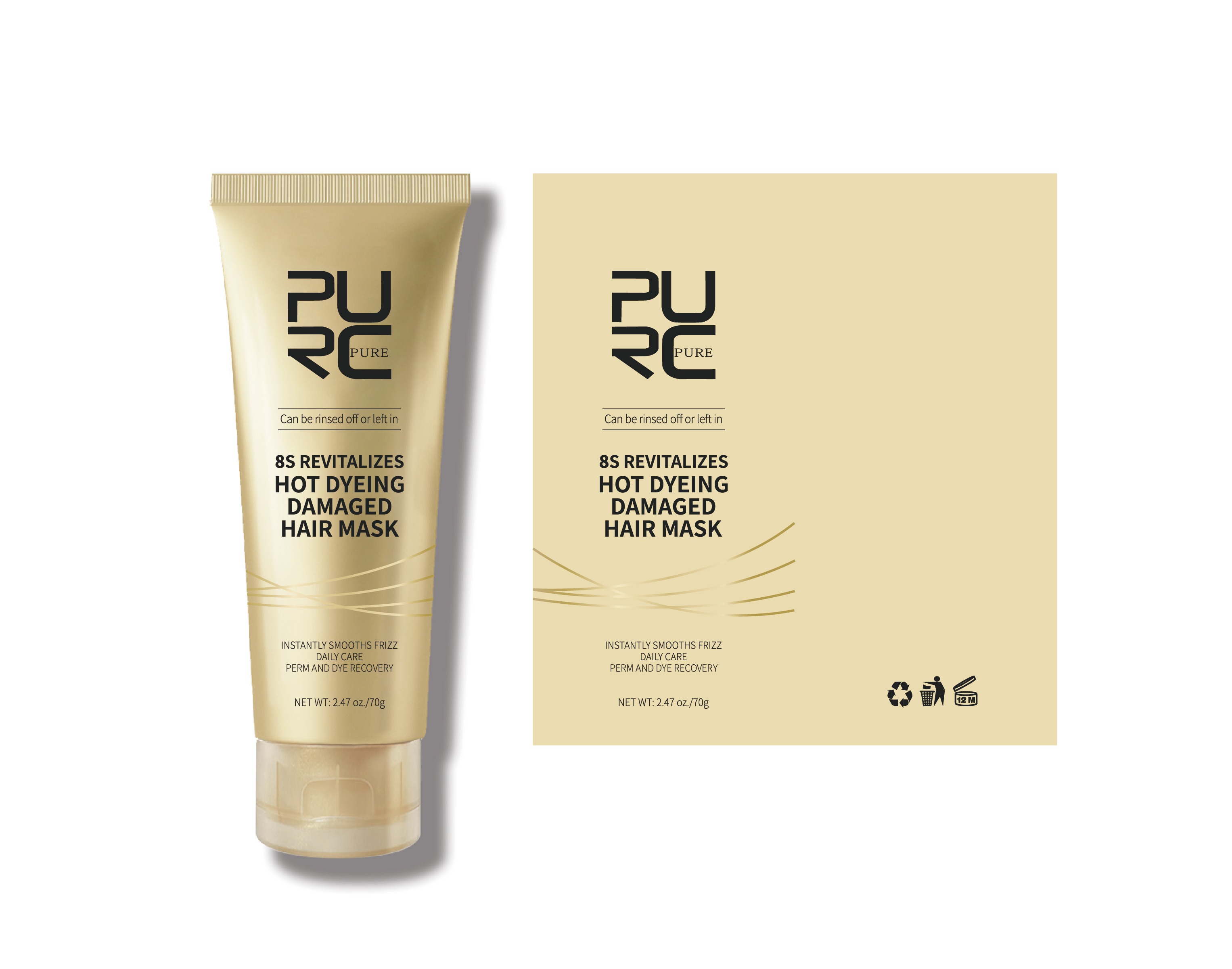 DRUG LABEL: PURC DISULFIDE BOND REDUCTIVE HAIR MASK
NDC: 84186-004 | Form: CREAM
Manufacturer: Guangzhou Bonnieco Cosmetics Co., Ltd
Category: otc | Type: HUMAN OTC DRUG LABEL
Date: 20240319

ACTIVE INGREDIENTS: JOJOBA OIL 10 g/100 g
INACTIVE INGREDIENTS: CETOSTEARYL ALCOHOL; TRIMETHYL OCTADECYL AMMONIUM CHLORIDE; CETEARYL STEARATE; STEARDIMONIUM HYDROXYPROPYL PEG-7 DIMETHICONE PHOSPHATE CHLORIDE; WATER; POLYAMINOPROPYL BIGUANIDE; ALOE VERA LEAF; AMODIMETHICONE (800 CST); TRIDECETH-12; AMINOPROPYL DIMETHICONE (1000 MPA.S); DISPERSE RED 15

84186-004

Active Ingredient

SIMMONDSIA CHINENSIS (JOJOBA) SEED OIL 10%

Purpose

Rejuvenating disulfide bonds
Recombinant hair core
Strong and resilient hair strands.

Use

Squeeze out and apply gently to hair

Warnings

For external use only. Keep out of reach of children

When Using

·In case of sensitive skin, please test the product on the inside of the arm first. Discontinue use if signs of irritation or rash occur and seek the assistance of a dermatologist.
·Avoid contact with eyes, In case of contact with the eyes, rinse immediately with plenty of water.

Keep Oot Of Reach Of Children

If swallowed, get medical help or contact a poison control center right away.

Directions

Before washing your hair, wet your hair with clean water and then towel-dry it until it's semi-dry. Take an appropriate amount of the product and evenly apply it to your hair strands, gently massaging it in to ensure better absorption. Allow the hair mask to stay on the hair for approximately 3 minutes, and then rinse it off thoroughly with plenty of clean water.

Other information

PRE-WASH USE

HIGHLIGHTS: The product contains hydrolyzed keratin and Silsoft AX fluid, professional hair rejuvenate ingredients. With just one application,it can instantly rejuvenate damaged disulfide bonds in the hair, making it stronger and less prone to breakage It also helps restructure the hair back to a healthier state, reducing hair loss during shampooing and restoring the shine, smoothness, and resilience of the hair to achieve a healthier and more vibrant appearance.

Inactive ingredients

WATER, CETEARYL ALCOHOL, ALOE BARBADENSIS LEAF JUICE, BIS-CETEARYL AMODIMETHICONE, BIS-AMINOPROPYL DIMETHICONE, STEARTRIMONIUM CHLORIDE, AMODIMETHICONE, PARFUM, STEARDIMONIUM HYDROXYPROPYL HYDROLYZED KERATIN, TRIDECETH-12, POLYAMINOPROPYL BIGUANIDE